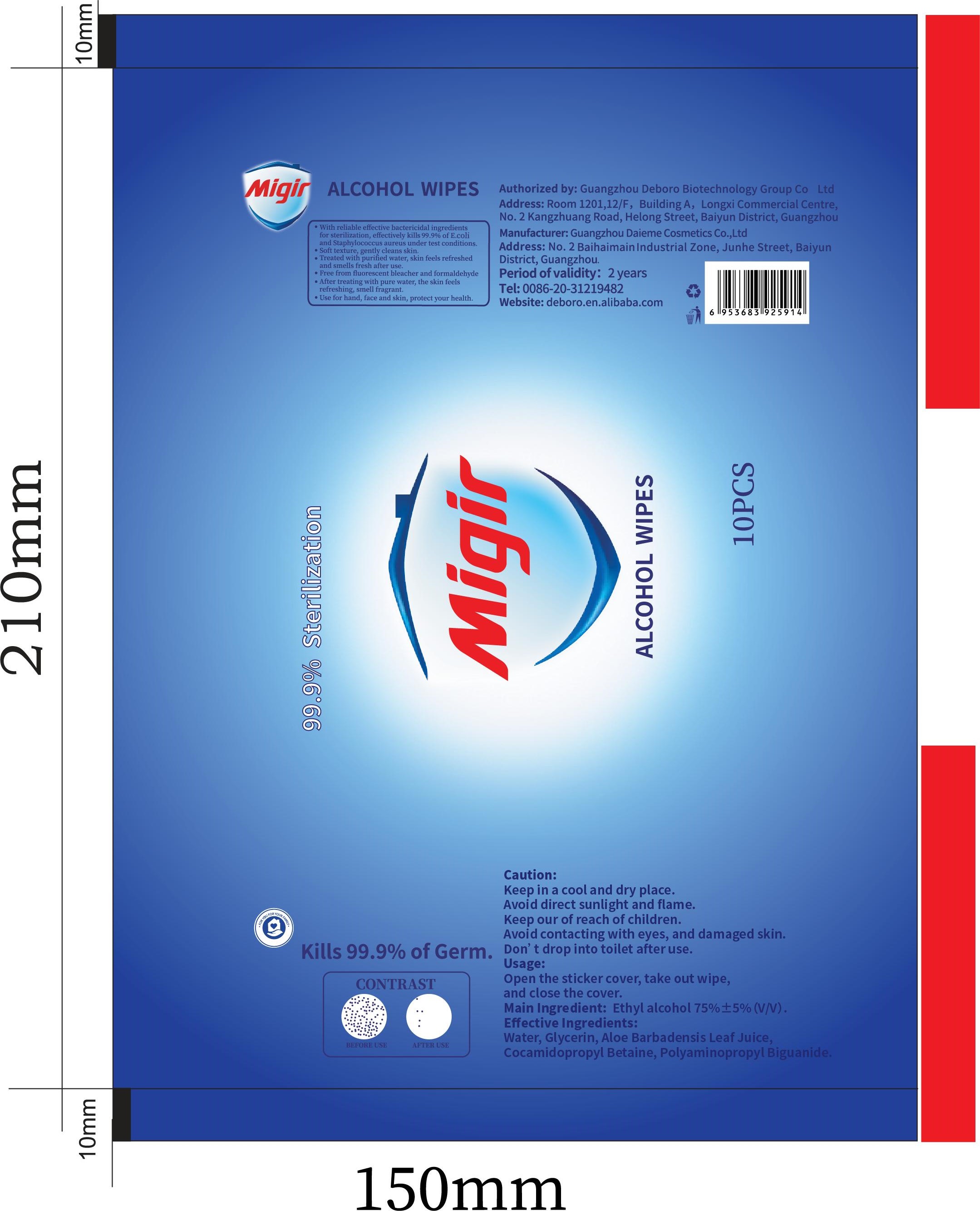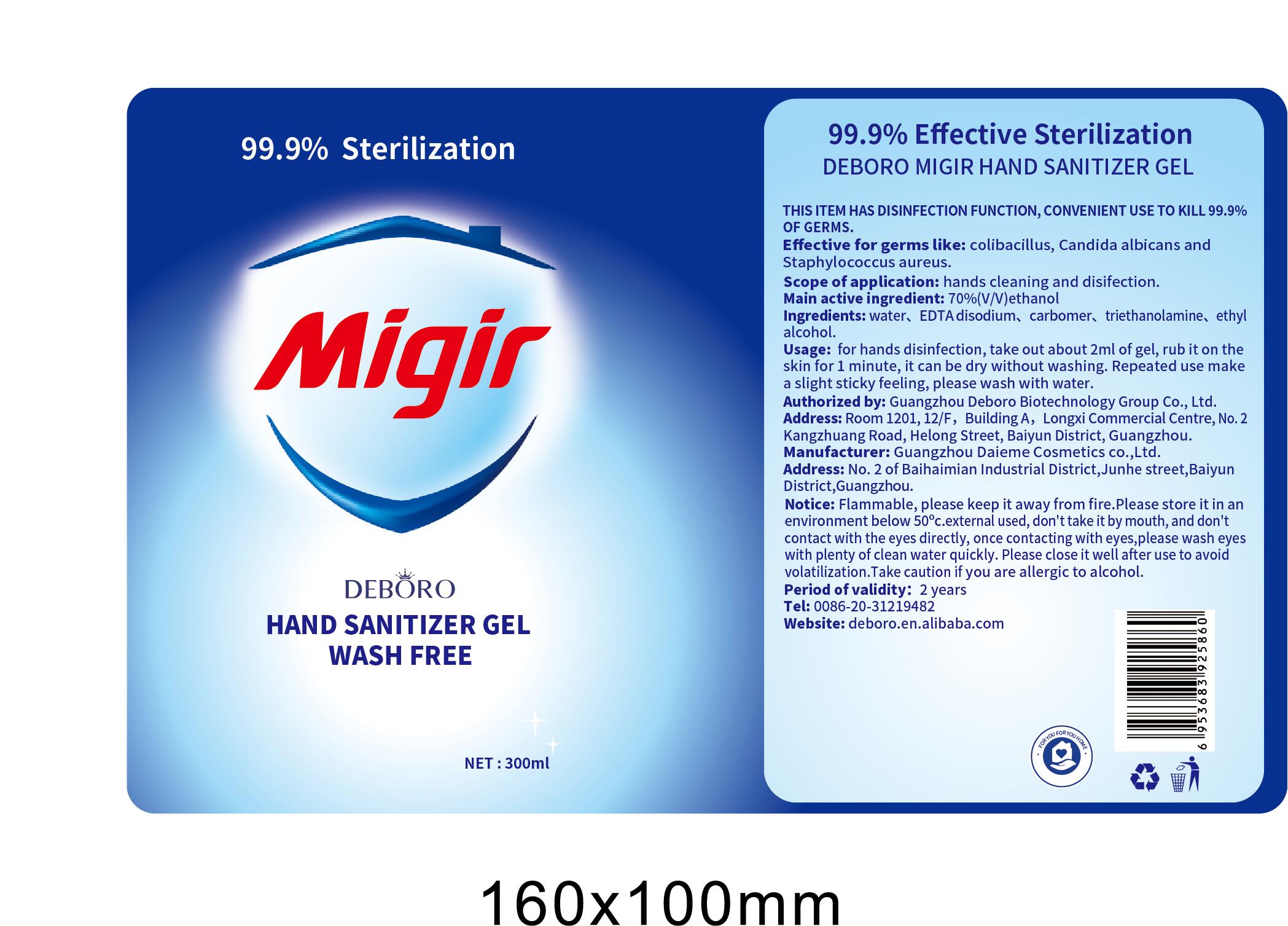 DRUG LABEL: Alcohol wet wipe
NDC: 54237-031 | Form: GEL
Manufacturer: Guangzhou Daieme Cosmetic Co,.Ltd
Category: otc | Type: HUMAN OTC DRUG LABEL
Date: 20210202

ACTIVE INGREDIENTS: ALCOHOL 72.7 mL/100 mL
INACTIVE INGREDIENTS: POLYAMINOPROPYL BIGUANIDE 0.5 mL/100 mL; GLYCERIN 1 mL/100 mL; WATER

Main active ingredient

70%(v/v) ethanol

- THIS ITEM HAS DISINFECTION FUNCTION, CONVENIENT USE TO KILL 99.9% OF GERMS.
- Effective for germs like: colibasillus. Candida albicans anc Staphylococcus aureus.
- Scope of application: hands cleaning and disifection.
- Main active ingredient: 70%(V/V)ethanol
- Ingredients: water, EDTA disodium, carbomer, triethanolamine, ethyalcohol.
- Usage: for hands disinfection, take out about 2ml of gel, rub it on the skin for 1 minute, it can be dry without washing. Repeated use make a slight sticky feeling, please wash with water.
- Notice: Flammable, please keep it away from fire.Please store it in an environment below 50℃.external used, don't take it by mouth, and don't contact with the eyes directly, once contacting with eyes,please wash eyes with plenty of clean water quickly. Please close it well after use to avoid volatilization.Take caution if you are allergic to alcohol.
- Period of validity: 2 years

Scope of application

Hands cleaning and disifection

Usage

for hands disinfection, take out about 2ml of gel, rub it on the skin for 1 minute, it can be dry without washing. Repeated use make a slight sticky feeling, please wash with water.

Notice

Flammable, please keep it away from fire.Please store it in an environment below 50℃.external used, don'ttake it by mouth, and don't contact with the eyes directly, once contacting with eyes,please wash eyes with plenty of clean water quickly. Please close it well after use to avoid volatilization.Take caution if you are allergic to alcohol.

Do not use

- Avoid contacting with eyes, and damaged skin

WHEN USING

Flammable, please keep it away from fire.Please store it in an environment below 50°c.external used, don'ttake it by mouth, and don't contact with the eyes directly, once contacting with eyes,please wash eyes with plenty of clean water quickly. Please close it well after use to avoid volatilization.Take caution if you are allergic to alcohol.

STOP USE

Take caution if you are allergic to alcohol.

KEEP OUT OF REACH OF CHILDREN

Keep our of reach of children. Avoid contacting with eyes, and damaged skin

Directions

Avoid contacting with eyes, and damaged skin

Other information

- Please store it in an environment below 50 ℃

ingredients

water, EDTA disodium, carbomer, triethanolamine, ethyl alcohol.